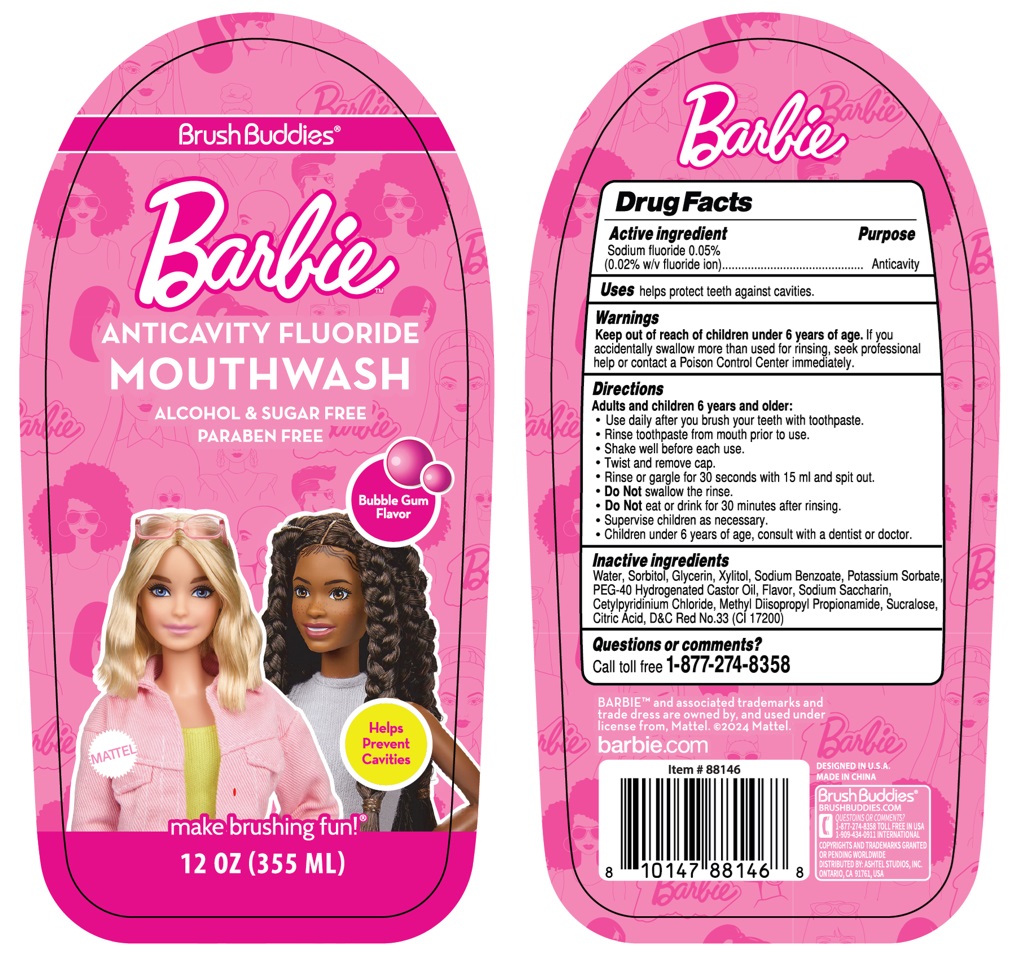 DRUG LABEL: Brush Buddies Barbie ANTICAVITY FLUORIDE - Bubble Gum Flavor
NDC: 70108-094 | Form: MOUTHWASH
Manufacturer: Ashtel Studios Inc.
Category: otc | Type: HUMAN OTC DRUG LABEL
Date: 20240731

ACTIVE INGREDIENTS: SODIUM FLUORIDE 0.05 g/100 mL
INACTIVE INGREDIENTS: WATER; SORBITOL; GLYCERIN; XYLITOL; SODIUM BENZOATE; POTASSIUM SORBATE; POLYOXYL 40 HYDROGENATED CASTOR OIL; SACCHARIN SODIUM; CETYLPYRIDINIUM CHLORIDE; METHYL DIISOPROPYL PROPIONAMIDE; SUCRALOSE; CITRIC ACID MONOHYDRATE; D&C RED NO. 33

Brush Buddies® Barbie ANTICAVITY FLUORIDE MOUTHWASH

Active ingredient

Sodium fluoride 0.05%
(0.02% w/v fluoride ion)

Purpose

Anticavity

Uses

helps protect teeth against cavities.

Warnings

Keep out of reach of children under 6 years of age. If you accidentally swallow more than used for rinsing, seek professional help or contact a Poison Control Center immediately.

Directions

Adults and children 6 years and older:
• Use daily after you brush your teeth with toothpaste.
• Rinse toothpaste from mouth prior to use.
• Shake well before each use.
• Twist and remove cap.
• Rinse or gargle for 30 seconds with 15 ml and spit out.
• Do not swallow the rinse.
• Do not eat or drink for 30 minutes after rinsing.
• Supervise children as necessary.
• Children under 6 years of age, consult with a dentist or doctor.

Inactive ingredients

Water, Sorbitol, Glycerin, Xylitol, Sodium Benzoate, Potassium Sorbate, PEG-40 Hydrogenated Castor Oil, Flavor, Sodium Saccharin, Cetylpyridinium Chloride, Methyl Diisopropyl Propionamide, Sucralose, Citric Acid, D&C Red No.33 (CI 17200)

Questions or comments?

Call toll free 1-877-274-8358

ALCOHOL & SUGAR FREE

PARABEN FREE

MATTEL

Helps Prevent Cavities
make brushing fun!®

BARBIE™ and associated trademarks and trade dress are owned by, and used under license from, Mattel. ©2024 Mattel.
barbie.com

DESIGNED IN U.S.A.
MADE IN CHINA

Brush Buddies®

BRUSHBUDDIES.COM

1-909-434-0911 INTERNATIONAL
COPYRIGHTS AND TRADEMARKS GRANTED OR PENDING WORLDWIDE
DISTRIBUTED BY: ASHTEL STUDIOS, INC. ONTARIO, CA 91761, USA